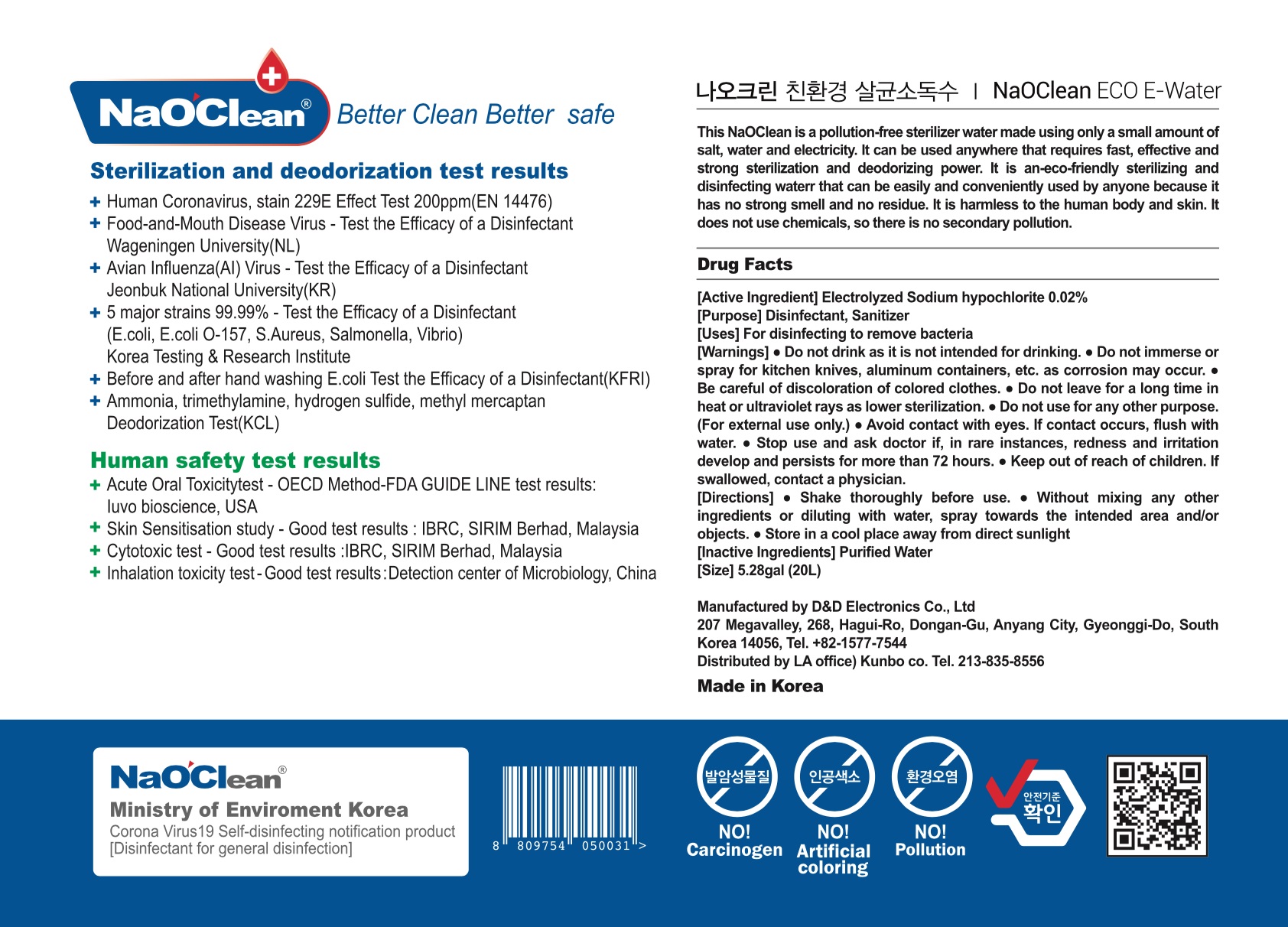 DRUG LABEL: NaOClean E-Water
NDC: 76876-0002 | Form: LIQUID
Manufacturer: D&D Electronics Co Ltd
Category: otc | Type: HUMAN OTC DRUG LABEL
Date: 20200807

ACTIVE INGREDIENTS: SODIUM HYPOCHLORITE 0.02 g/100 mL
INACTIVE INGREDIENTS: WATER

Drug Facts

ACTIVE INGREDIENT

Sodium hypochlorite

PURPOSE

For disinfecting to remove bacteria

KEEP OUT OF REACH OF THE CHILDREN

INDICATIONS AND USAGE

● Shake thoroughly before use.

● Without mixing any other ingredients or diluting with water, spray towards the intended area and/or objects.

● Store in a cool place away from direct sunlight

WARNINGS

● Do not drink as it is not intended for drinking.

● Do not immerse or spray for kitchen knives, aluminum containers, etc. as corrosion may occur.

● Be careful of discoloration of colored clothes.

● Do not leave for a long time in heat or ultraviolet rays as lower sterilization.

● Do not use for any other purpose. (For external use only.)

● Avoid contact with eyes. If contact occurs, flush with water.

● Stop use and ask doctor if, in rare instances, redness and irritation develop and persists for more than 72 hours.

● Keep out of reach of children. If swallowed, contact a physician.

DOSAGE AND ADMINISTRATION

for external use only

INACTIVE INGREDIENT

water